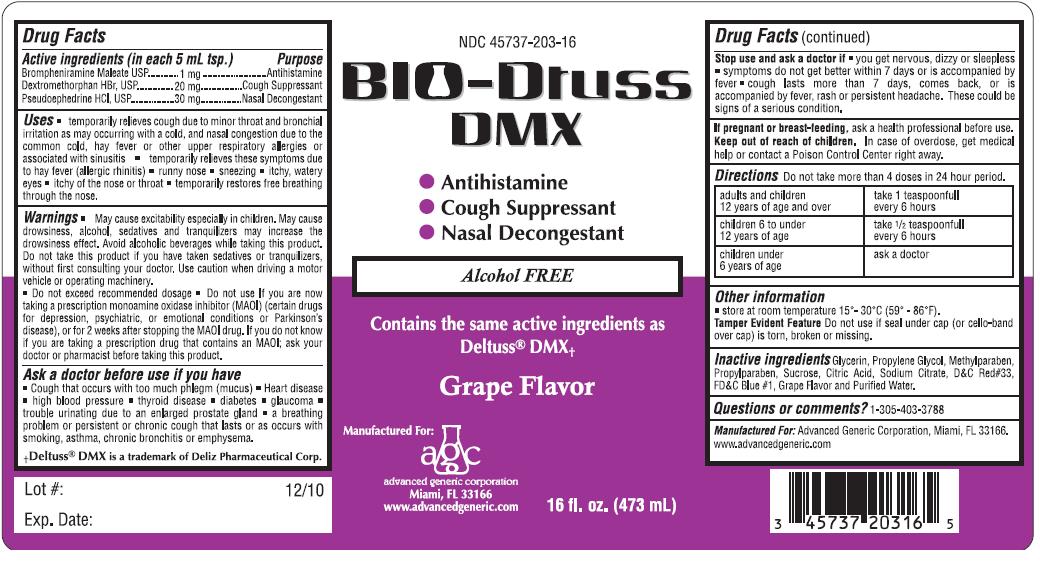 DRUG LABEL: BIO Dtuss
NDC: 45737-203 | Form: LIQUID
Manufacturer: Advanced Generic Corporation
Category: otc | Type: HUMAN OTC DRUG LABEL
Date: 20241220

ACTIVE INGREDIENTS: BROMPHENIRAMINE MALEATE 1 mg/5 mL; DEXTROMETHORPHAN HYDROBROMIDE 20 mg/5 mL; PSEUDOEPHEDRINE HYDROCHLORIDE 30 mg/5 mL
INACTIVE INGREDIENTS: GLYCERIN; PROPYLENE GLYCOL; METHYLPARABEN; PROPYLPARABEN; SUCROSE; CITRIC ACID MONOHYDRATE; SODIUM CITRATE; WATER

AGC- BioDTussDMX 203

Active Ingredients(in each 5 mL tsp.) Purpose
Brompheniramine Maleate...................... 1mg ..................................Antihistamine
Dextromethorphen HBr........................... 20 mg ............................Cough Suppressant
Pseudoephedrine HCl............................. 30mg .............................Nasal Decongestant

Uses:

- Temporarily relieves cough due to minor throat and bronchial irritation as may occurring with a cold, and nasal congestion due to the common cold, hay fever or other upper respiratory allergies or associated with sinusitis
- Temporarily relieves these symptoms due to hay fever(allergies rhinitis)
- Runny nose
- Sneezing
- Itchy, watery eyes
- Itchy of the nose or throat
- Temporarily restores free breathing through the nose

Warnings:

- May cause excitability especially in children. May cause drowsiness, alcohol, sedatives and tranquilizers may increase the drowsiness effect. Avoid alcohol beverages while taking this product. Do not take this product if you have taken sedatives or tranquilizers, without first consulting your doctor. Use caution when driving a motor vehicle or operating machinery.
- Do not exceed recommended dosage. Do not use if you are now taking a prescription monoamine oxidase inhibitor (MAOI) (certain drugs for depression, psychiatric, or emotional conditions or Parkinson's disease), or for 2 weeks after stopping the MAOI drug. If you do not know if you are taking a prescription drug that contains an MAOI; ask your doctor or pharmacist before taking this product.

Do Not Use:

Ask a doctor before use if you have:

- Cough that occurs with too much phlegm (mucus)
- Heart disease
- High blood pressure
- Thyroid disease
- Diabetes
- Glaucoma
- Trouble urinating due to an enlarged prostate gland
- A breathing problem or persistent or chronic cough that lasts or as occurs with smoking, asthma, chronic bronchitis or emphysema

Stop use and ask a doctor if:

- You get nervous, dizzy or sleepless
- Symptoms do not get better within 7 days, comes back, or is accompaniend by fever, rash or persistent headache. These could be signs of a serious condition

Keep out of reach of children.In case of overdose, get medical help or contact a Poison Control Center right away.

PREGNANCY OR BREAST FEEDING

If pregnant or breast-feeding,ask a health professional before use.

Directions:

adults and children 12 years of age and over | take 1 teaspoonfull every 6 hours
children 6 to under 12 years of age | take 1/2 teaspoonfull every 6 hours
children under 6 years of age | ask doctor

Other Information:

store at room temperature 15-30 degrees celcius (59-86 degrees farenheit)

Tamper Evident FeatureDo not use if seal under cap(or cello band over cap) is torn, broken or missing

Inactive Ingredients:

Glycerin, Propylene Glycol, Methylparaben, Propylparaben, Sucrose, Citric Acid, Sodium Citrate, D and C Red #33, FD and C Blue #1, Grape Flavor and Purified Water.

QUESTIONS

Question and Comments?1-305-403-3788

Advanced Generic Corporation, Miami, FL 33166

www.advancedgeneric.com